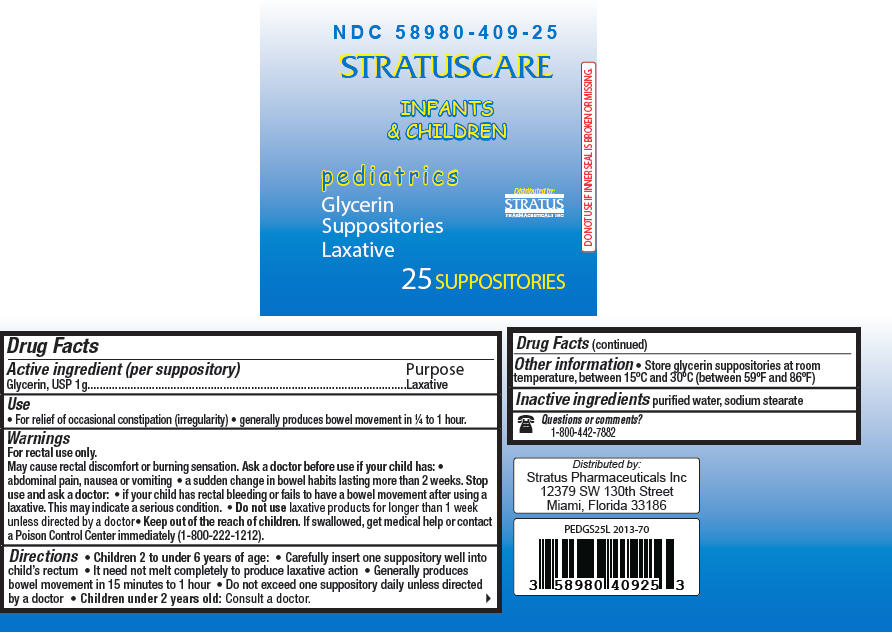 DRUG LABEL: Stratuscare Glycerin Laxative Pediatric
NDC: 58980-409 | Form: SUPPOSITORY
Manufacturer: Stratus Pharmaceuticals
Category: otc | Type: HUMAN OTC DRUG LABEL
Date: 20241101

ACTIVE INGREDIENTS: Glycerin 1 g/1 1
INACTIVE INGREDIENTS: Water; SODIUM STEARATE

Stratuscare Glycerin Suppositories Laxative Pediatric

Drug Facts

Active ingredient (per suppository)

Glycerin, USP 1g

Purpose

Laxative

Use

- For relief of occasional constipation (irregularity)
- generally produces bowel movement in ¼ to 1 hour.

Warnings

For rectal use only.

May cause rectal discomfort or burning sensation.

Ask a doctor before use if your child has:

- abdominal pain, nausea or vomiting
- a sudden change in bowel habits lasting more than 2 weeks.

Stop use and ask a doctor:

- if your child has rectal bleeding or fails to have a bowel movement after using a laxative. This may indicate a serious condition.

- Do not use laxative products for longer than 1 week unless directed by a doctor

KEEP OUT OF REACH OF CHILDREN

- Keep out of the reach of children. If swallowed, get medical help or contact a Poison Control Center immediately (1-800-222-1212).

Directions

- Children 2 to under 6 years of age:
  - Carefully insert one suppository well into child's rectum
  - It need not melt completely to produce laxative action
  - Generally produces bowel movement in 15 minutes to 1 hour
  - Do not exceed one suppository daily unless directed by a doctor
- Children under 2 years old: Consult a doctor.

Other information

- Store glycerin suppositories at room temperature, between 15°C and 30°C (between 59°F and 86°F)

Inactive ingredients

purified water, sodium stearate

Questions or comments?

1-800-442-7882

Distributed by:
Stratus Pharmaceuticals Inc
12379 SW 130th Street
Miami, Florida 33186

PRINCIPAL DISPLAY PANEL - 25 Suppository Jar Label

NDC 58980-409-25

STRATUSCARE

INFANTS
& CHILDREN

pediatrics
Glycerin
Suppositories
Laxative

Distributed by:
STRATUS
PHARMACEUTICALS INC

25 SUPPOSITORIES

DO NOT USE IF INNER SEAL IS BROKEN OR MISSING.